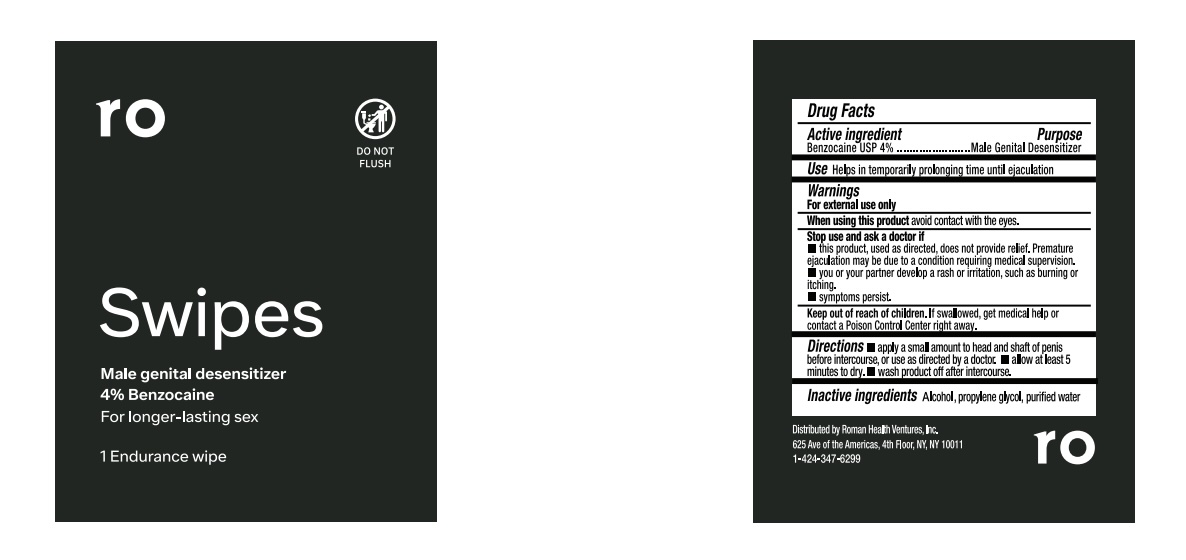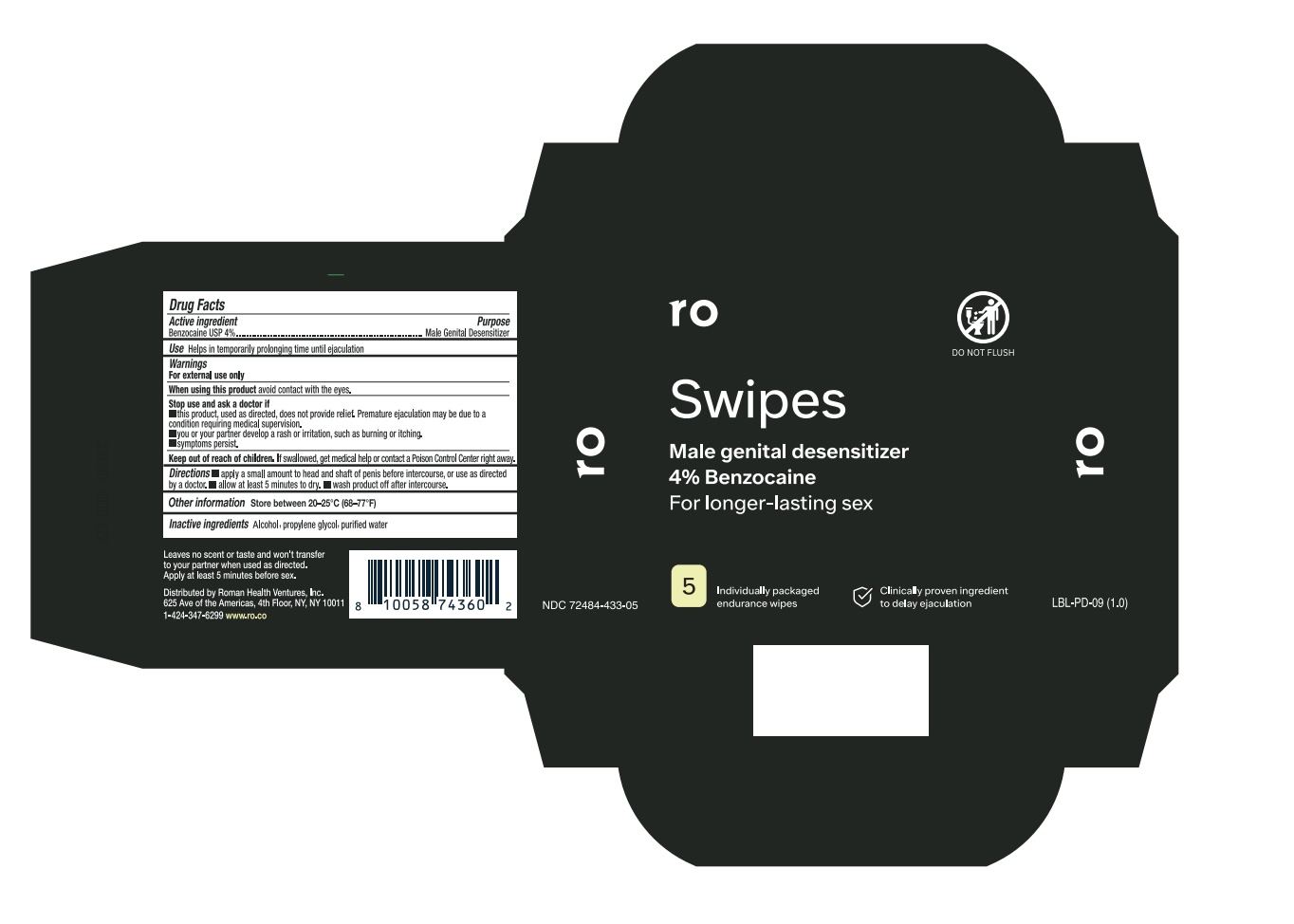 DRUG LABEL: Roman Swipes
NDC: 72484-433 | Form: LIQUID
Manufacturer: Roman Health Ventures Inc.
Category: otc | Type: HUMAN OTC DRUG LABEL
Date: 20250212

ACTIVE INGREDIENTS: BENZOCAINE 4 g/100 mL
INACTIVE INGREDIENTS: ALCOHOL; WATER; PROPYLENE GLYCOL

Roman Swipes

Drug Facts

Active ingredient

Benzocaine USP 4%

Purpose

Male Genital Desensitizer

Use

Helps in temporarily prolonging time until ejaculation

Warnings

For external use only

When using this product avoid contact with the eyes.

Stop use and ask a doctor if

- this product, used as directed, does not provide relief. Premature ejaculation may be due to a condition requiring medical supervision.
- you or your partner develop a rash or irritation, such as burning or itching
- symptoms persist.

Keep out of reach of children. If swallowed, get medical help or contact a poison control center right away.

Directions

- Apply a small amount to head and shaft of penis before intercourse, or use as directed by a doctor.
- Allow at least 5 minutes to dry
- Wash product off after intercourse.

Added "Allow at least 5 minutes to dry" to instructions

Allow at least 5 minutes to dry

INACTIVE INGREDIENT

Inactive ingredients ethyl alcohol (SDA 40B), propylene glycol, purified water

Distributed by Roman Health Ventures, Inc.

116 W. 23rd Street, 4th Floor, New York, NY 10011

888-798-8686 getroman.com

PACKAGE LABEL

roman

SWIPES

with 4% Benzocaine

For longer lasting sex

8 INDIVIDUALLY PACKAGED ENDURANCE WIPES

CLINICALLY PROVEN INGREDIENT TO DELAY EJACULATION